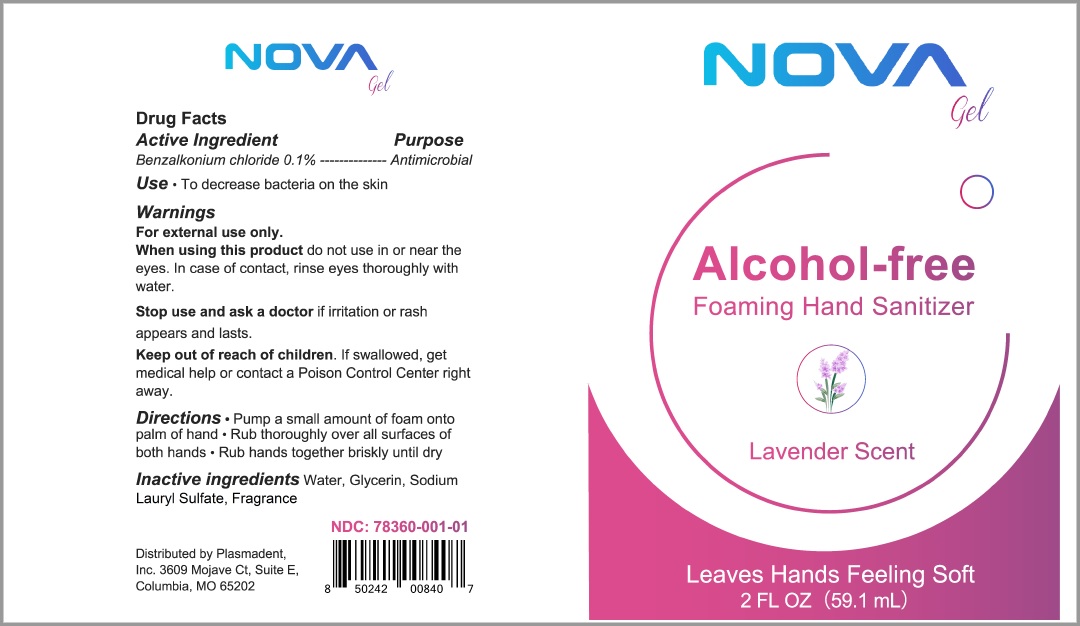 DRUG LABEL: NovaGel Alcohol-free Foaming Hand Sanitizer
NDC: 78360-001 | Form: LIQUID
Manufacturer: Zhejiang Hongshiliang Health Technology Co Ltd
Category: otc | Type: HUMAN OTC DRUG LABEL
Date: 20200428

ACTIVE INGREDIENTS: BENZALKONIUM CHLORIDE 0.1 g/100 g
INACTIVE INGREDIENTS: WATER 97.1 g/100 g; GLYCERIN 2 g/100 g; SODIUM LAURYL SULFATE 0.5 g/100 g

Principle Display Panel

Active Ingredient

Active Ingredient Purpose

Benzalkonium chloride 0.1% Antimicrobial

Use

To decrease bacteria on skin

Keep out of reach of children- If swallowed, get medical help or contact a Poison Control Center right away.

Warning

Warnings. For external use only.

When using this product do not use in or near the eyes. In case of contact, rinse eyes thoroughly with water.

Stope use and ask a doctor if irritation or rash appears and lasts.

Keep out of reach of children. If swallowed, get medical help or contact a poison control center right away.

Directions

Directions - Pump a small amount of foam onto palm of hand. Rub thoroughly over all surfaces of both hands. Rub hands together briskly until dry.

Inactive ingredients

Inactive ingredients- water, glycerin, sodium lauryl sulfate, fragrance

Dosage and Adminstration Section

Benzalkonium Chloride 0.1%

Directions - Pump a small amount of foam onto palm of hand. Rub thoroughly over all surfaces of both hands. Rub hands together briskly until dry.

Purpose Section

Purpose

Antimicrobial